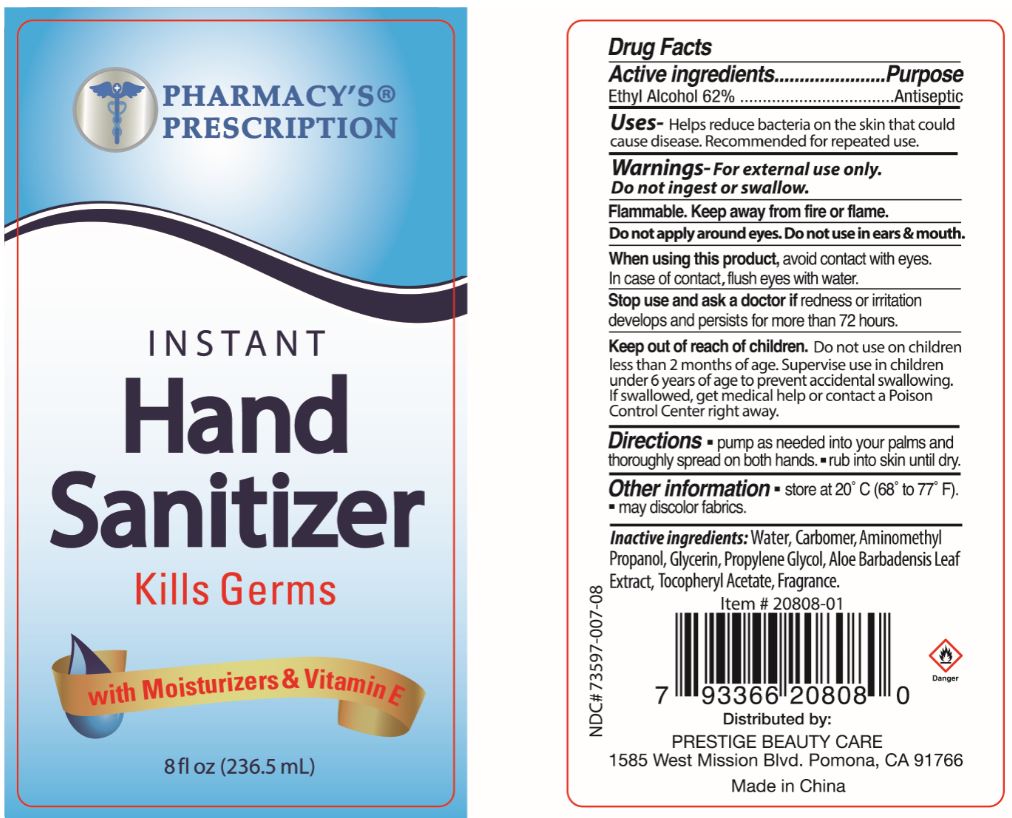 DRUG LABEL: Pharmacys Prescription Hand Sanitizer
NDC: 73597-007 | Form: GEL
Manufacturer: Mission Series Inc. dba Prestige Beauty Care
Category: otc | Type: HUMAN OTC DRUG LABEL
Date: 20200514

ACTIVE INGREDIENTS: ALCOHOL 62 mL/100 mL
INACTIVE INGREDIENTS: WATER; AMINOMETHYLPROPANOL; PROPYLENE GLYCOL; .ALPHA.-TOCOPHEROL ACETATE; CARBOMER HOMOPOLYMER, UNSPECIFIED TYPE; GLYCERIN; ALOE VERA LEAF

Pharmacys Prescription Hand Sanitizer

Active Ingredients

Active ingredents - Ethyl Alcohol 62%

Purpose

Purpose - Antiseptic

Indications & Usage

Uses - Helps reduce bacteria on the skin that could cause disease. Recommended for repeated use.

Warnings

Warnings - For external use only.

Do not ingest or swallow.

Flammable. Keep away from fire or flame.

Do not apply around eyes. Do not use in ears & mouth.

When using this product, avoid contact with eyes.

In case of contact, flush eyes with water.

Stop use

Stop use and ask a doctor if redness or irritation develops and persists for more than 72 hours.

Keep out of reach of children. Do not use on children less than 2 months of age. Supervise use in children under 6 years of age to prevent accidental swallowing. If swallowed, get medical help or contact a Poison Control Center right away.

Directions

Directions - pump as needed into your palms and thoroughly spread on both hands - rub into skin until dry.

Other information

Other information - store at 20°C (68° to 77° F).

-may discolor fabrics.

Inactive Ingredients

Inactive ingredients: Water, Carbomer, Aminomethyl Propanol, Glycerin, Propylene Glycol, Aloe Barbadensis Leaf Extract, Tocopheryl Acetate, Fragrance.

Distributed by:

PRESTIGE BEAUTY CARE

1585 West Mission Blvd.

Pomona, CA 91766

Made in China